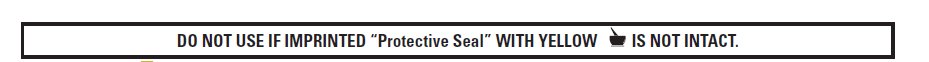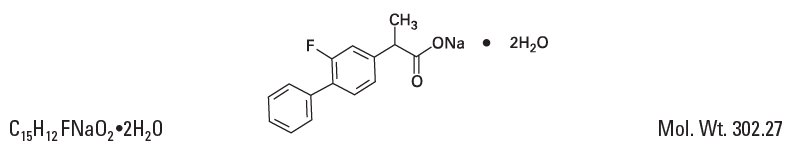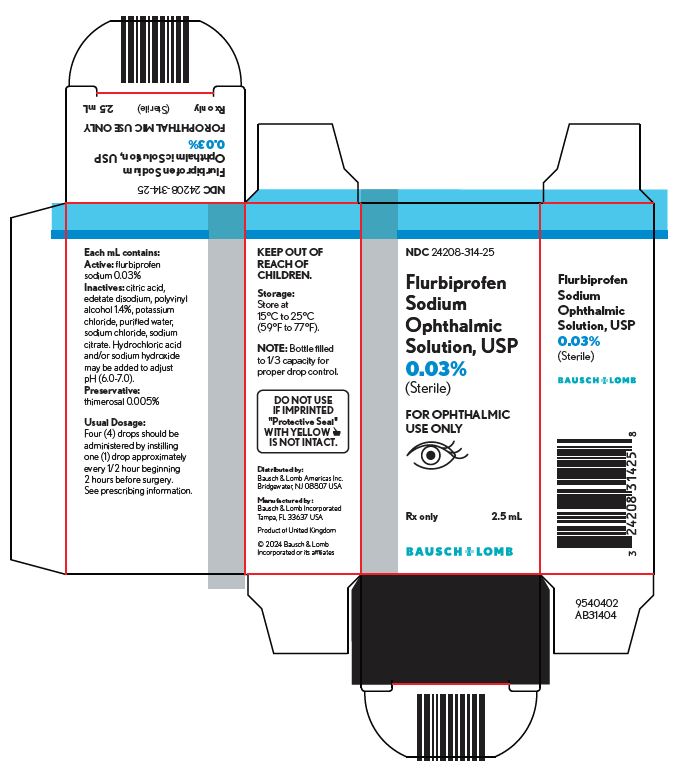 DRUG LABEL: Flurbiprofen Sodium
NDC: 24208-314 | Form: SOLUTION/ DROPS
Manufacturer: Bausch & Lomb Incorporated
Category: prescription | Type: HUMAN PRESCRIPTION DRUG LABEL
Date: 20240724

ACTIVE INGREDIENTS: FLURBIPROFEN SODIUM 0.3 mg/1 mL
INACTIVE INGREDIENTS: CITRIC ACID MONOHYDRATE; EDETATE DISODIUM; HYDROCHLORIC ACID; POTASSIUM CHLORIDE; WATER; SODIUM CHLORIDE; SODIUM CITRATE, UNSPECIFIED FORM; SODIUM HYDROXIDE; THIMEROSAL; POLYVINYL ALCOHOL, UNSPECIFIED

Flurbiprofen Sodium Ophthalmic Solution, USP 0.03%
(Sterile)

Rx only

FOR OPHTHALMIC USE ONLY

DESCRIPTION

Flurbiprofen sodium ophthalmic solution USP, 0.03% is a sterile topical nonsteroidal anti-inflammatory product for ophthalmic use.

Chemical Name:
Sodium (±)-2-(2-fluoro-4-biphenylyl)propionate dihydrate.

Structural Formula:

Each mL contains:

Active: flurbiprofen sodium 0.03%.

Inactives: citric acid, edetate disodium, polyvinyl alcohol 1.4%, potassium chloride, purified water, sodium chloride, sodium citrate. Hydrochloric acid and/or sodium hydroxide may be added to adjust pH (6.0 – 7.0).

Preservative: thimerosal 0.005%.

CLINICAL PHARMACOLOGY

Flurbiprofen sodium is one of a series of phenylalkanoic acids that have shown analgesic, antipyretic, and anti-inflammatory activity in animal inflammatory diseases. Its mechanism of action is believed to be through inhibition of the cyclo-oxygenase enzyme that is essential in the biosynthesis of prostaglandins.

Prostaglandins have been shown in many animal models to be mediators of certain kinds of intraocular inflammation. In studies performed on animal eyes, prostaglandins have been shown to produce disruption of the blood-aqueous humor barrier, vasodilatation, increased vascular permeability, leukocytosis, and increased intraocular pressure.

Prostaglandins also appear to play a role in the miotic response produced during ocular surgery by constricting the iris sphincter independently of cholinergic mechanisms. In clinical studies, flurbiprofen sodium ophthalmic solution has been shown to inhibit the miosis induced during the course of cataract surgery.

Results from clinical studies indicate that flurbiprofen sodium has no significant effect upon intraocular pressure.

INDICATIONS AND USAGE

Flurbiprofen sodium ophthalmic solution is indicated for the inhibition of intraoperative miosis.

CONTRAINDICATIONS

Flurbiprofen sodium ophthalmic solution is contraindicated in individuals who are hypersensitive to any components of the medication.

WARNINGS

With some nonsteroidal anti-inflammatory drugs, there exists the potential for increased bleeding time due to interference with thrombocyte aggregation. There have been reports that flurbiprofen sodium ophthalmic solution may cause increased bleeding of ocular tissues (including hyphemas) in conjunction with ocular surgery.

There is the potential for cross-sensitivity to acetylsalicylic acid and other nonsteroidal anti-inflammatory drugs. Therefore, caution should be used when treating individuals who have previously exhibited sensitivities to these drugs.

PRECAUTIONS

General

Topical nonsteroidal anti-inflammatory drugs (NSAIDs) may slow or delay healing. Topical corticosteroids are also known to slow or delay healing. Concomitant use of topical NSAIDs and topical steroids may increase the potential for healing problems.

It is recommended that flurbiprofen sodium ophthalmic solution be used with caution in surgical patients with known bleeding tendencies or who are receiving other medications which may prolong bleeding time.

Information for Patients

Patients should be instructed to avoid allowing the tip of the bottle to contact the eye or surrounding structures because this could cause the tip to become contaminated by common bacteria known to cause ocular infections. Serious damage to the eye and subsequent loss of vision may result from using contaminated solutions.

To avoid the potential for cross-contamination, the patient should be advised to use one bottle for each eye with bilateral ocular surgery. The use of the same bottle of eye drops for both eyes is not recommended with ocular surgery.

Drug Interactions

Interaction of flurbiprofen sodium ophthalmic solution with other topical ophthalmic medications has not been fully investigated.

Although clinical studies with acetylcholine chloride and animal studies with acetylcholine chloride or carbachol revealed no interference, and there is no known pharmacological basis for an interaction, there have been reports that acetylcholine chloride and carbachol have been ineffective when used in patients treated with flurbiprofen sodium ophthalmic solution.

Carcinogenesis, Mutagenesis, Impairment of Fertility

Long-term studies in mice and/or rats have shown no evidence of carcinogenicity with flurbiprofen.

Long-term mutagenicity studies in animals have not been performed.

Pregnancy

Flurbiprofen has been shown to be embryocidal, delay parturition, prolong gestation, reduce weight, and/or slightly retard growth of fetuses when given to rats in daily oral doses of 0.4 mg/kg (approximately 300 times the human daily topical dose) and above. There are no adequate and well-controlled studies in pregnant women. Flurbiprofen sodium ophthalmic solution should be used during pregnancy only if the potential benefit justifies the potential risk to the fetus.

Nursing Mothers:

It is not known whether this drug is excreted in human milk. Because many drugs are excreted in human milk and because of the potential for serious adverse reactions in nursing infants from flurbiprofen sodium, a decision should be made whether to discontinue nursing or to discontinue the drug, taking into account the importance of the drug to the mother.

Pediatric Use

Safety and effectiveness in pediatric patients have not been established.

Geriatric Use

No overall differences in safety or effectiveness have been observed between elderly and younger patients.

ADVERSE REACTIONS

Transient burning and stinging upon instillation and other minor symptoms of ocular irritation have been reported with the use of flurbiprofen sodium ophthalmic solution. Other adverse reactions reported with the use of flurbiprofen sodium ophthalmic solution include: fibrosis, hyphema, miosis, mydriasis, and ocular hyperemia.

Increased bleeding tendency of ocular tissues in conjunction with ocular surgery has also been reported [see Warnings].

To report SUSPECTED ADVERSE REACTIONS, contact Bausch & Lomb Incorporated at 1-800-553-5340 or FDA at 1-800-FDA-1088 or www.fda.gov/medwatch.

OVERDOSAGE

Overdosage will not ordinarily cause acute problems. If accidentally ingested, drink fluids to dilute.

DOSAGE AND ADMINISTRATION

A total of four (4) drops of flurbiprofen sodium ophthalmic solution should be administered by instilling one (1) drop approximately every 1/2 hour beginning 2 hours before surgery.

HOW SUPPLIED

Flurbiprofen sodium ophthalmic solution USP, 0.03% is supplied in a plastic bottle with a controlled drop tip in the following size:

2.5 mL - NDC 24208-314-25

Storage:

Store at 15°C to 25°C (59°F to 77°F).

Distributed by:
Bausch & Lomb Americas Inc.
Bridgewater, NJ 08807 USA

Manufactured by:
Bausch & Lomb Incorporated
Tampa, FL 33637 USA
© 2022 Bausch & Lomb Incorporated or its affiliates
Revised: September 2022

9100605 (Folded)

9100705 (Flat)

Principal Display Panel

NDC24208-314-25

Flurbiprofen
Sodium
Ophthalmic
Solution, USP
0.03%
(Sterile)

FOR OPHTHALMIC
USE ONLY

Rx only

2.5 mL

BAUSCH + LOMB

9540402
AB31404